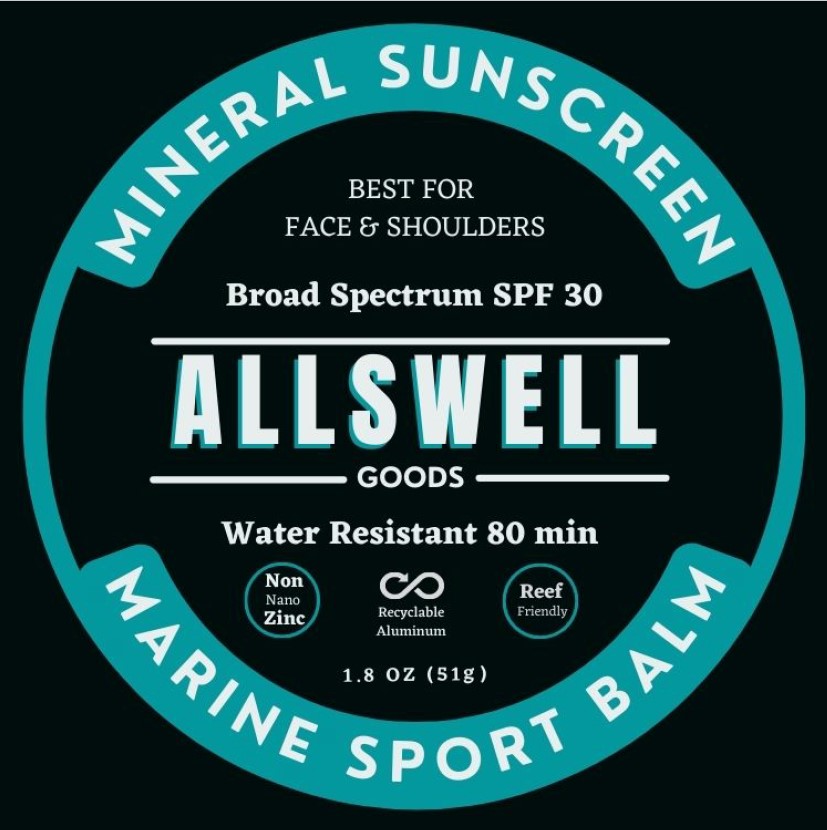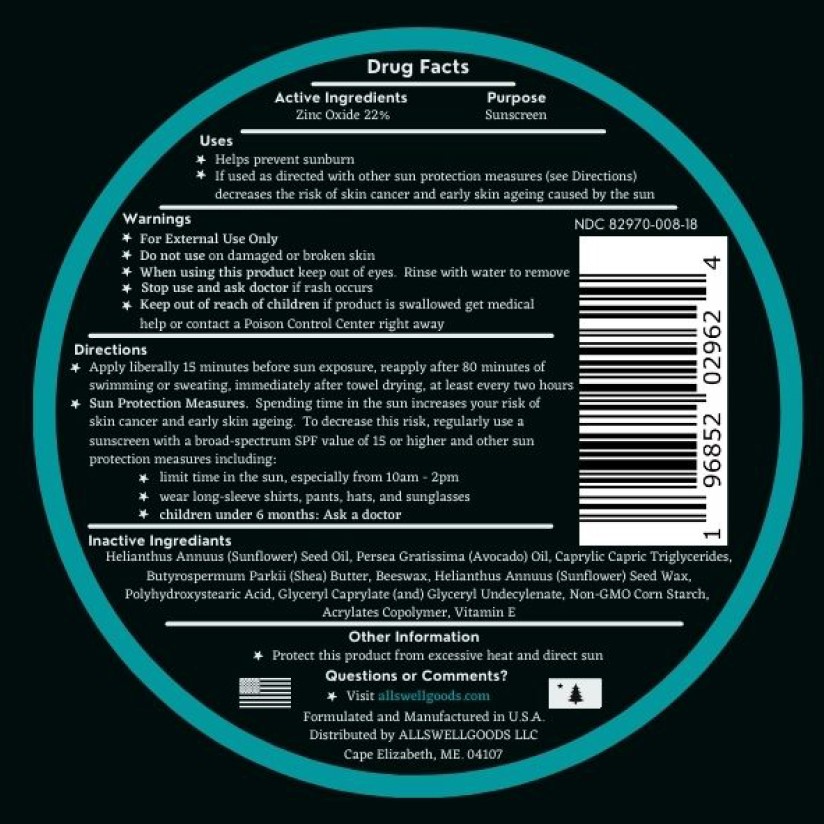 DRUG LABEL: ALLSWELL MINERAL SUNSCREEN SPF 30
NDC: 69555-043 | Form: LOTION
Manufacturer: Stream2Sea, LLC
Category: otc | Type: HUMAN OTC DRUG LABEL
Date: 20250112

ACTIVE INGREDIENTS: ZINC OXIDE 22 g/1 1
INACTIVE INGREDIENTS: SUNFLOWER OIL; AVOCADO OIL; MEDIUM-CHAIN TRIGLYCERIDES; SHEA BUTTER; YELLOW WAX; HELIANTHUS ANNUUS SEED WAX; POLYHYDROXYSTEARIC ACID (2300 MW); GLYCERYL CAPRYLATE; GLYCERYL 1-UNDECYLENATE; STARCH, CORN; BUTYL ACRYLATE/METHYL METHACRYLATE/METHACRYLIC ACID COPOLYMER (18000 MW); .ALPHA.-TOCOPHEROL

ALLSWELL MINERAL SUNSCREEN SPF 30

Active ingredient

Zinc Oxide 22%

Purpose

Sunscreen

Uses

- Helps prevent sunburn.
- If used as directed with other sun protection measures (See Directions), decreases the risk of skin cancer and early skin aging caused by the sun.

Warnings

- For external use only
- Do not use on damaged or broken skin.
- When using this product, keep out of eyes. Rinse with water to remove.
- Stop use and ask a doctor if rash occurs.
- Keep out of reach of children. If product swallowed get medical help or contact a Poison Control Center right away.

Directions

- Apply liberally 15 minutes before sun exposure, reapply after 80 minutes of swimming or sweating, immediately after towel drying, at least every two hours
- Sun Protection Measures. Spending time in the sun increases your risk of skin cancer and early skin aging. To decrease this risk, regularly use a sunscreen with a broad-spectrum SPF value of 15 or higher and other sun protection measures including:
  - limit time in the sun, especially from 10am – 2pm
  - wear long-sleeve shirts, pants, hats and sunglasses
  - Children under 6 months: Ask a doctor

Inactive Ingredients

Helianthus Annus (Sunflower) Seed Oil, Persea Gratissima (Avocado) Oil, Caprylic Capric Triglycerides, Butyrospermum Parkii (Shea) Butter, Beeswax, Helianthus Annus (Sunflower) Seed Wax, Polyhydroxystearic Acid, Glyceryl Caprylate (and) Glyceryl Undecylenate, Non-GMO Corn Starch, Acrylates Copolymer, Vitamin E

Other Information

- Protect this product from excessive heat and direct sun

Questions or comments?

- Visit allswellgoods.com

PACKAGE LABEL

Allswell Mineral Sunscreen Spf 30-NDC 69555-043-01-Tube label